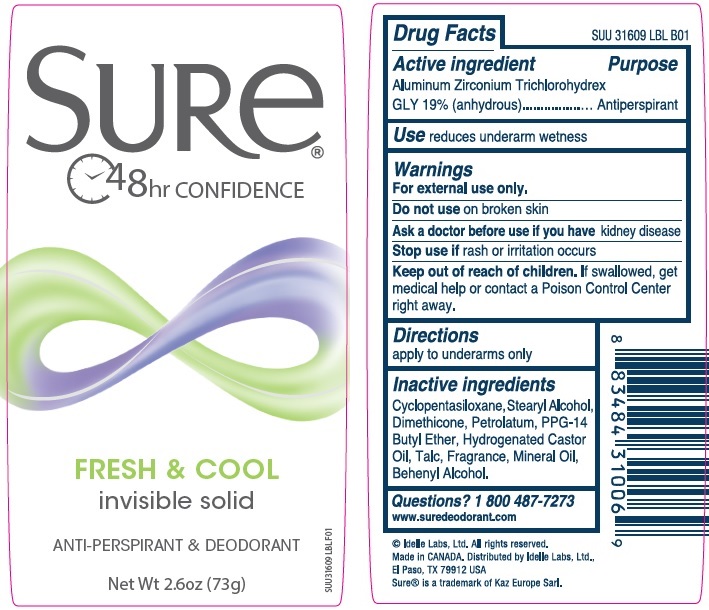 DRUG LABEL: Sure Invisible Solid Fresh and Cool
NDC: 41595-5545 | Form: STICK
Manufacturer: Idelle Labs, Ltd
Category: otc | Type: HUMAN OTC DRUG LABEL
Date: 20210820

ACTIVE INGREDIENTS: ALUMINUM ZIRCONIUM TRICHLOROHYDREX GLY 19 g/100 g
INACTIVE INGREDIENTS: CYCLOMETHICONE 5; STEARYL ALCOHOL; DIMETHICONE; PETROLATUM; PPG-14 BUTYL ETHER; HYDROGENATED CASTOR OIL; TALC; MINERAL OIL; DOCOSANOL

Sure Invisible Solid Fresh and Cool Antiperspirant Deodorant

SURe®

48hr CONFIDENCE

FRESH & COOL

invisible solid

ANTI-PERSPIRANT & DEODORANT

Net Wt 2.6oz (73g)

Drug Facts

Active ingredient

Aluminum Zirconium Trichlorohydrex GLY 19% (anhydrous)

Purpose

Antiperspirant

Use

Reduces underarm wetness

Warnings

For external use only.

Do not use

On broken skin

Ask a doctor before use if you have

kidney disease

Stop use if

Rash or irritation occurs

Keep out of reach of children.

If swallowed, get medical help or contact a Poison Control Center right away.

Directions

Apply to underarms only

Inactive ingredients

Cyclopentasiloxane, Stearyl Alcohol, Dimethicone, Petrolatum, PPG-14 Butyl Ether, Hydrogenated Castor Oil, Talc, Fragrance, Mineral Oil, Behenyl Alcohol.

Questions?

1 800-487-7273
www.suredeodorant.com
© Idelle Labs, Ltd. All rights reserved.
Made in CANADA. Distributed by Idelle Labs, Ltd.,
El Paso, TX 79912 USA
Sure® is a trademark of Kaz Europe Sarl.